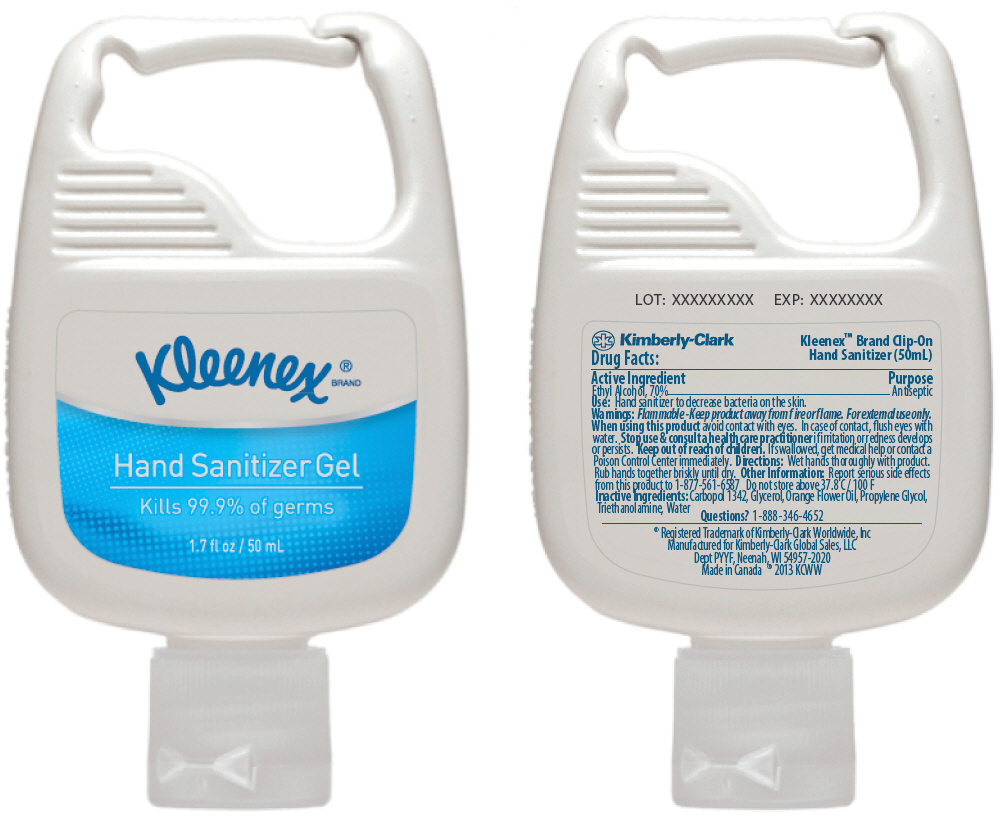 DRUG LABEL: KLEENEX Hand Sanitizer
NDC: 55118-610 | Form: SOLUTION
Manufacturer: Kimberly-Clark Corporation
Category: otc | Type: HUMAN OTC DRUG LABEL
Date: 20141103

ACTIVE INGREDIENTS: Alcohol 70 mL/100 mL
INACTIVE INGREDIENTS: Carbomer Copolymer Type B (Allyl Pentaerythritol Crosslinked); Glycerin; Citrus Sinensis Flower Oil; Propylene Glycol; Trolamine; Water

KLEENEX® Hand Sanitizer Gel

Active Ingredient

Ethyl Alcohol, 70%

Purpose

Antiseptic

Use

Hand sanitizer to decrease bacteria on the skin.

Warnings

Flammable - Keep product away from fire or flame. For external use only.

When using this product avoid contact with eyes. In case of contact, flush eyes with water.

Stop use & consult a health care practitioner if irritation or redness develops or persists.

Keep out of reach of children. If swallowed, get medical help or contact a Poison Control Center immediately.

Directions

Wet hands thoroughly with product. Rub hands together briskly until dry.

Other Information

Report serious side effects from this product to 1-877-561-6587 Do not store above 37.8 C / 100 F

Inactive Ingredients

Carbopol 1342, Glycerol, Orange Flower Oil, Propylene Glycol, Triethanolamine, Water

Questions?

1-888-346-4652

PRINCIPAL DISPLAY PANEL - 50 mL Bottle Label

Kleenex ® BRAND

Hand Sanitizer Gel

Kills 99.9% of germs

1.7 fl oz / 50 mL